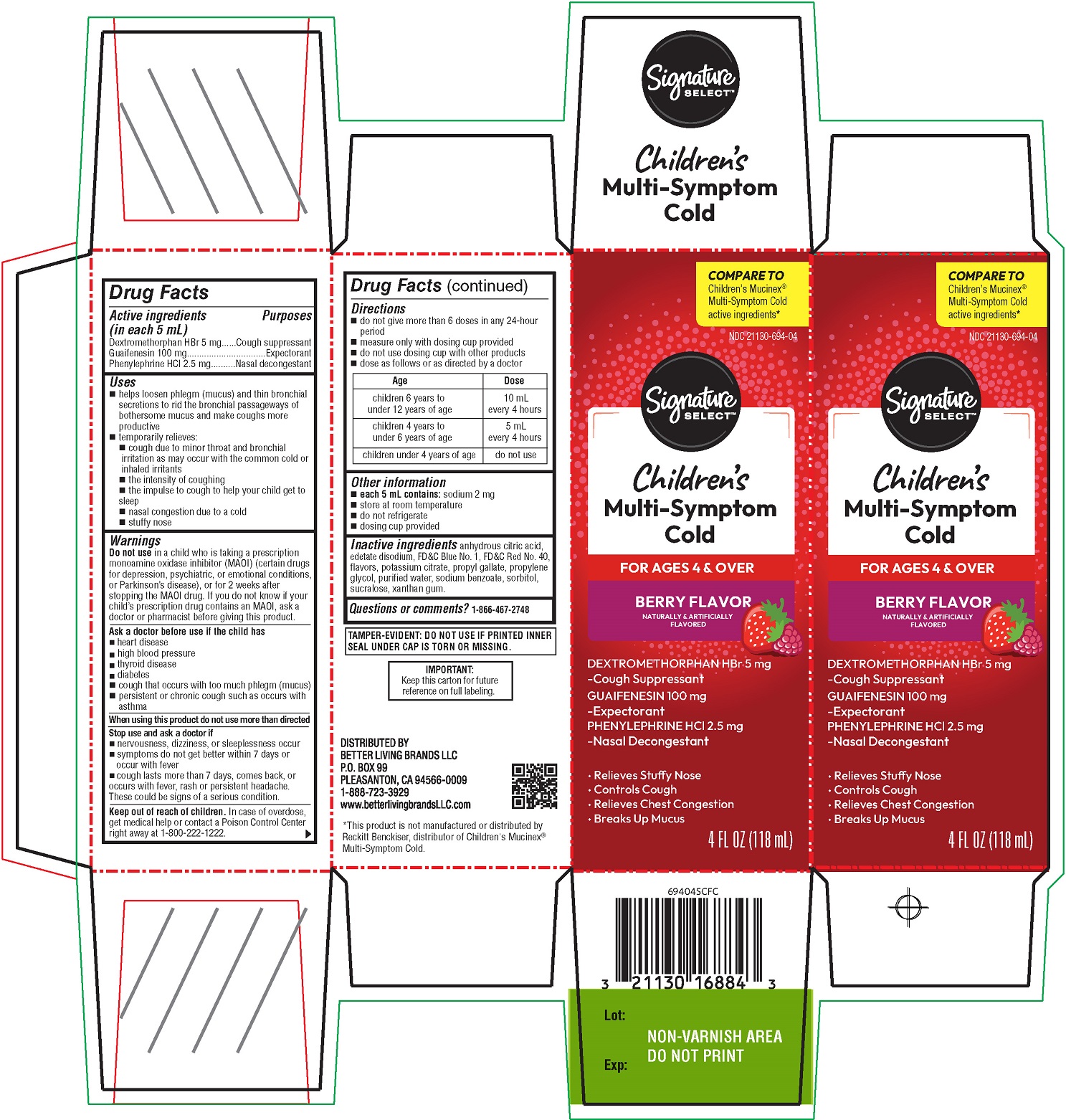 DRUG LABEL: SIGNATURE CARE
NDC: 21130-162 | Form: SOLUTION
Manufacturer: SAFEWAY
Category: otc | Type: HUMAN OTC DRUG LABEL
Date: 20260211

ACTIVE INGREDIENTS: DEXTROMETHORPHAN HYDROBROMIDE 5 mg/5 mL; GUAIFENESIN 100 mg/5 mL; PHENYLEPHRINE HYDROCHLORIDE 2.5 mg/5 mL
INACTIVE INGREDIENTS: ANHYDROUS CITRIC ACID; EDETATE DISODIUM; FD&C BLUE NO. 1; FD&C RED NO. 40; TRISODIUM CITRATE DIHYDRATE; PROPYL GALLATE; PROPYLENE GLYCOL; WATER; SODIUM BENZOATE; SORBITOL; SUCRALOSE; XANTHAN GUM

SC Children's Multi-Symptom Cold

Drug Facts

ACTIVE INGREDIENT

PURPOSE

Active ingredients (in each 5 mL) | Purposes
Dextromethorphan HBr 5 mg | Cough suppressant
Guaifenesin 100 mg | Expectorant
Phenylephrine HCl 2.5 mg | Nasal decongestant

Uses

- helps loosen phlegm (mucus) and thin bronchial secretions to rid the bronchial passageways of bothersome mucus and make coughs more productive
- temporarily relieves:
  - cough due to minor throat and bronchial irritation as may occur with the common cold or inhaled irritants
  - the intensity of coughing
  - the impulse to cough to help your child get to sleep
  - nasal congestion due to a cold
  - stuffy nose

Warnings

Do not use in a child who is taking a prescription monoamine oxidase inhibitor (MAOI) (certain drugs for depression, psychiatric, or emotional conditions, or Parkinson's disease), or for 2 weeks after stopping the MAOI drug. If you do not know if your child's prescription drug contains an MAOI, ask a doctor or pharmacist before giving this product.

Ask a doctor before use if the child has

- heart disease
- high blood pressure
- thyroid disease
- diabetes
- cough that occurs with too much phlegm (mucus)
- persistent or chronic cough such as occurs with asthma

When using this product do not use more than directed

Stop use and ask a doctor if

- nervousness, dizziness or sleeplessness occur
- symptoms do not get better within 7 days or occur with fever
- cough lasts more than 7 days, comes back, or occurs with fever, rash, or persistent headache. These could be signs of a serious condition.

Keep out of reach of children. In case of overdose, get medical help or contact a Poison Control Center right away at 1-800-222-1222.

Directions

- do not take more than 6 doses in any 24-hour period
- measure only with dosing cup provided
- do not use dosing cup with other products
- dose as follows or as directed by a doctor

Age | Dose
children 6 years to under 12 years | 10 mL every 4 hours
children 4 years to under 6 years | 5 mL every 4 hours
children under 4 years | do not use

Other information

- each 5 mL contains: sodium 2 mg
- store at room temperature
- do not refrigerate
- dosing cup provided

Inactive ingredients

anhydrous citric acid, edetate disodium, FD&C Blue No.1, FD&C Red #40, flavors, potassium citrate. propyl gallate, propylene glycol, purified water, sodium benzoate, sorbitol, sucralose, xanthan gum

Questions or comments?

1-866-467-2748

DISTRIBUTED BY

BETTER LIVING BRANDS LLC

P.O. BOX 99

PLEASANTON, CA 94566-0009

1-888-723-3929

www.betterlivingbrandsLLC.com

PRINCIPAL DISPLAY PANEL

COMPARE TO ChildrenMucinex® Multi-Symptom Cold active ingredients*

NDC 21130-162-04

Signature SELECT

Children’s Multi-Symptom Cold

FOR AGES 4 & OVER

BERRY FLAVOR

NATURALLY & ARTIFICIALLY FLAVORED

Dextromethorphan HBr 5 mg - Cough Suppressant
Guaifenesin 100 mg - Expectorant
Phenylephrine HCl 2.5 mg - Nasal Decongestant

- Relieves Stuffy Nose
- Controls Cough
- Relieves Chest Congestion
- Breaks up Mucus

4 FL OZ (118 mL)

TAMPER EVIDENT: DO NOT USE IF NECKBAND ON BOTTLE CAP IS BROKEN OR MISSING.

IMPORTANT: Keep this carton for future reference on full labeling.

*This product is not manufactured or distributed by Reckitt Benckiser, distributor of Children’s Mucinex® Multi-Symptom Cold.